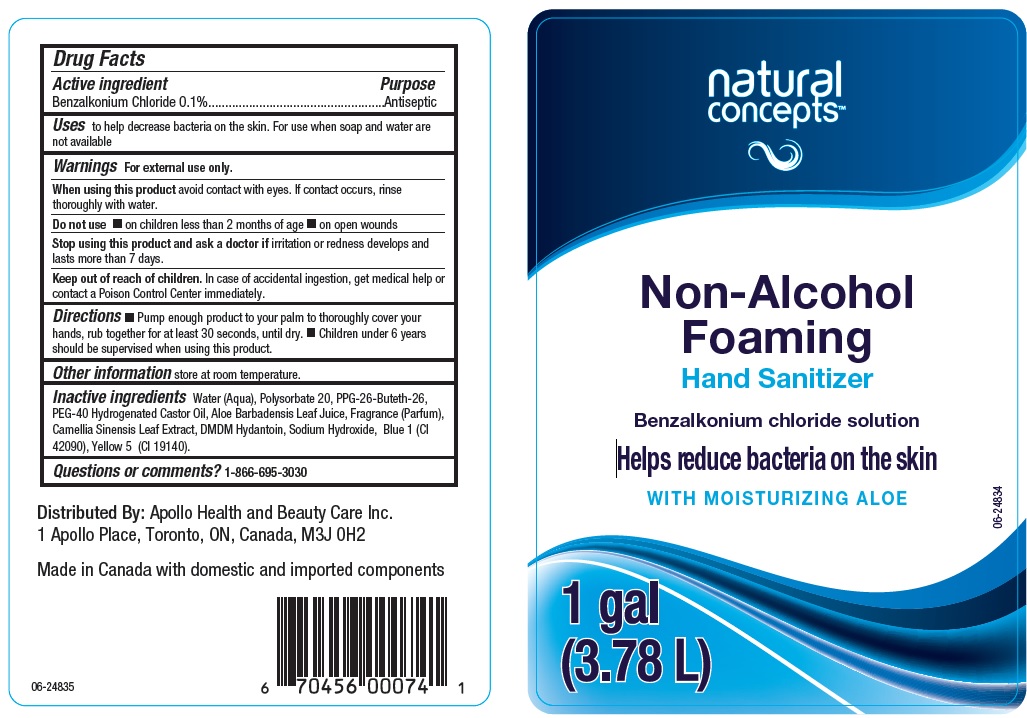 DRUG LABEL: Natural Concepts Non-Alcohol Foaming Hand Sanitizer
NDC: 63148-513 | Form: SOLUTION
Manufacturer: Apollo Health and Beauty Care Inc.
Category: otc | Type: HUMAN OTC DRUG LABEL
Date: 20200717

ACTIVE INGREDIENTS: BENZALKONIUM CHLORIDE 1 mg/1 mL
INACTIVE INGREDIENTS: WATER; POLYSORBATE 20; PPG-26-BUTETH-26; POLYOXYL 40 HYDROGENATED CASTOR OIL; ALOE VERA LEAF; GREEN TEA LEAF; DMDM HYDANTOIN; FD&C BLUE NO. 1; FD&C YELLOW NO. 5; SODIUM HYDROXIDE

Drug Facts

Active ingredient

Benzalkonium Chloride 0.1%

Purpose

Antiseptic

Uses

to help decrease bacteria on the skin. For use when soap and water are not available.

Warnings

For external use only.

When using this product

avoid contact with eyes. If contact occurs, rinse thoroughly with water.

Do not use

- on children less than 2 months of age
- on open wounds

Stop useing this product and ask a doctor if

irritation or redness develops and lasts more than 7 days.

Keep out of reach of children.

In case of accidental ingestion, get medical help or contact a Poison Control Center immediately.

Directions

- Pump enough product to your palm to thoroughly cover your hands, rub together for at least 30 seconds, until dry.
- Children under 6 years should be supervised when using this product.

Other information

store at room temperature.

Inactive ingredients

Water (Aqua), Polysorbate 20, PPG-26-Buteth-26, PEG-40 Hydrogenated Castor Oil, Aloe Barbadensis Leaf Juice, Fragrance (Parfum), Camellia Sinensis Leaf Extract, DMDM Hydantoin, Sodium Hydroxide, Blue 1 (CI 42090), Yellow 5 (CI 19140)

Questions or comments?

1-866-695-3030